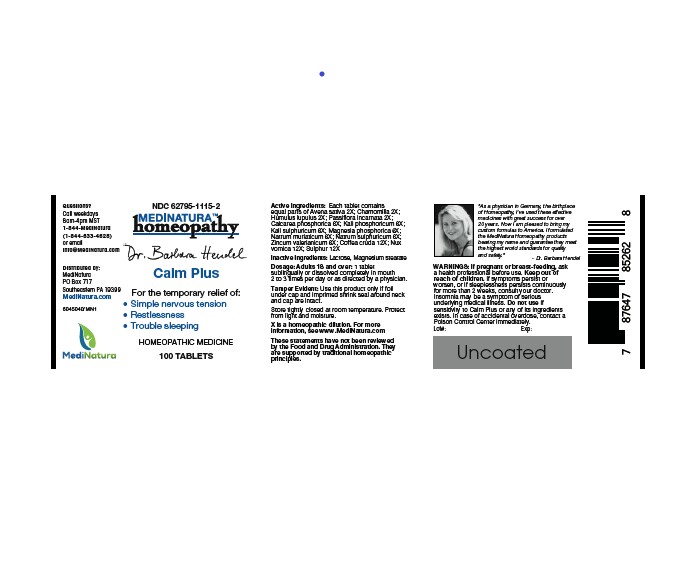 DRUG LABEL: Calm Plus
NDC: 62795-1115 | Form: TABLET
Manufacturer: MediNatura Inc
Category: homeopathic | Type: HUMAN OTC DRUG LABEL
Date: 20220818

ACTIVE INGREDIENTS: AVENA SATIVA FLOWERING TOP 2 [hp_X]/1 1; MATRICARIA RECUTITA 2 [hp_X]/1 1; PASSIFLORA INCARNATA FLOWERING TOP 2 [hp_X]/1 1; TRIBASIC CALCIUM PHOSPHATE 2 [hp_X]/1 1; DIBASIC POTASSIUM PHOSPHATE 6 [hp_X]/1 1; POTASSIUM SULFATE 6 [hp_X]/1 1; MAGNESIUM PHOSPHATE, DIBASIC 6 [hp_X]/1 1; SODIUM CHLORIDE 6 [hp_X]/1 1; SODIUM SULFATE 6 [hp_X]/1 1; ZINC VALERATE DIHYDRATE 6 [hp_X]/1 1; ARABICA COFFEE BEAN 12 [hp_X]/1 1; STRYCHNOS NUX-VOMICA SEED 12 [hp_X]/1 1; SULFUR 12 [hp_X]/1 1
INACTIVE INGREDIENTS: LACTOSE MONOHYDRATE; MAGNESIUM STEARATE

Dr. Hendel Calm Plus

WARNINGS

WARNINGS: If pregnant or breast-feeding, ask a health professional before use. Keep out of reach of children.

If symptoms persist or worsen, or if sleeplessness persists continuously for more than 2 weeks, consult your doctor.

Insomnia may be a symptom of serious underlying medical illness.

Do not use if sensitivity to Calm Plus or any of its ingredients exists. In case of accidental overdose, contact a Poison Control Center immediately.

KEEP OUT OF REACH OF CHILDREN

USES

For the temporary relief of:

• Simple nervous tension

• Restlessness

• Trouble sleeping

ACTIVE INGREDIENTS

Each tablet contains equal parts of Avena sativa 2X; Chamomilla 2X; Humulus lupulus 2X; Passiflora incarnata 2X; Calcarea phosphorica 6X; Kali phosphoricum 6X; Kali sulphuricum 6X; Magnesia phosphorica 6X; Natrum muriaticum 6X; Natrum sulphuricum 6X; Zincum valerianicum 6X; Coffea cruda 12X; Nux vomica 12X; Sulphur 12X

INACTIVE INGREDIENTS

Lactose, Magnesium stearate

DIRECTIONS

Dosage: Adults 18 and over: 1 tablet sublingually or dissolved completely in mouth 2 to 3 times per day or as directed by a physician.

PURPOSE

For the temporary relief of:

• Simple nervous tension

• Restlessness

• Trouble sleeping

PACKAGE LABEL

Add image transcription here...